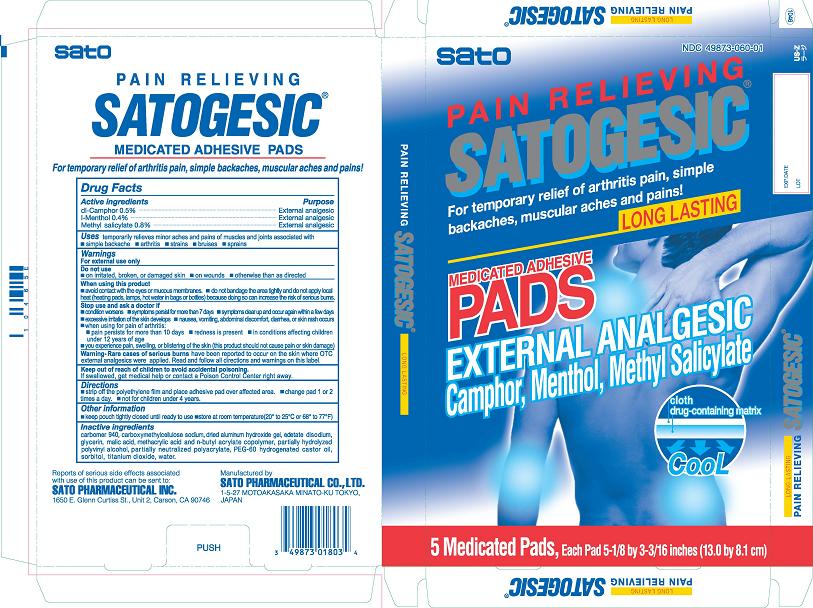 DRUG LABEL: Satogesic
NDC: 49873-060 | Form: PATCH
Manufacturer: Sato Pharmaceutical Co., Ltd.
Category: otc | Type: HUMAN OTC DRUG LABEL
Date: 20231109

ACTIVE INGREDIENTS: CAMPHOR (SYNTHETIC) 5 mg/1 1; LEVOMENTHOL 4 mg/1 1; METHYL SALICYLATE 8 mg/1 1
INACTIVE INGREDIENTS: CARBOXYMETHYLCELLULOSE SODIUM; POLYVINYL ALCOHOL; SORBITOL; GLYCERIN; TITANIUM DIOXIDE; EDETATE DISODIUM; MALIC ACID; WATER; POLYOXYL 60 HYDROGENATED CASTOR OIL; ALGELDRATE; BUTYL ACRYLATE/METHACRYLIC ACID COPOLYMER (2% METHACRYLIC ACID); CARBOMER 940; ACRYLIC ACID/SODIUM ACRYLATE COPOLYMER (1:1; 600 MPA.S AT 0.2%)

Satogessic Medicated Adhesive Pads

Active ingredients
dl-Camphor 0.5%
l-Menthol 0.4%
Methyl salicylate 0.8%

Purpose
dl-Camphor External analgesic
l-Menthol External analgesic
Methyl salicylate External analgesic

INDICATIONS AND USAGE

Uses temporary relieves minor aches and pains of muscles and joints associated with
■ simple backache ■ arthritis ■ strains ■ bruises ■ sprains

Warnings
For external use only

Do not use
■ on irritated, broken, or damaged skin ■ on wounds ■ otherwise than as directed

When using this product
■ avoid contact with the eyes or mucous membranes ■ do not bandage the area

tightly and do not apply local heat (heating pads, lamps, hot water in bags or bottles)

because doing so can increase the risk of serious burns

Stop use and ask a doctor if
■ condition worsens ■ symptoms persist for more than 7 days ■ symptoms clear up

and occur again within a few days

■ excessive irritation of the skin develops ■ nausea, vomiting,

abdominal discomfort, diarrhea, or skin rash occurs

■ when using for pain of arthritis:

■ pain persists for more than 10 days ■ redness is present ■ in conditions

affecting children under 12 years of age

■ you experience pain, swelling, or blistering of the skin (this product should not cause

pain or skin damage)

OTHER SAFETY INFORMATION

Warning - Rare cases of serious burns have been reported to occur on the skin where

OTC external analgesics were applied. Read and follow all directions and warnings on

this label.

Keep out of reach of children to avoid accidental poisoning. If swallowed, get medical

help or contact a Poison Control Center right away.

Directions
■ Strip off the polyethylene film and place adhesive pad over affected area. ■ Change pad 1 or 2 times a day
■ Not for children under 4 years.

Other Information
■ keep pouch tightly closed until ready to use ■ store at room temperature (20° to 25°C or 68° to 77°F)

Inactive ingredients
carbomer 940, carboxymethylcellulose sodium, dried aluminum hydroxide gel, edetate

disodium, glycerin, malic acid, methacrylic acid and n-butyl acrylate copolymer,

partially hydrolyzed polyvinyl alcohol, partially neutralized polyacrylate, PEG 60

hydrogenated castor oil, sorbitol, titanium dioxide, water.